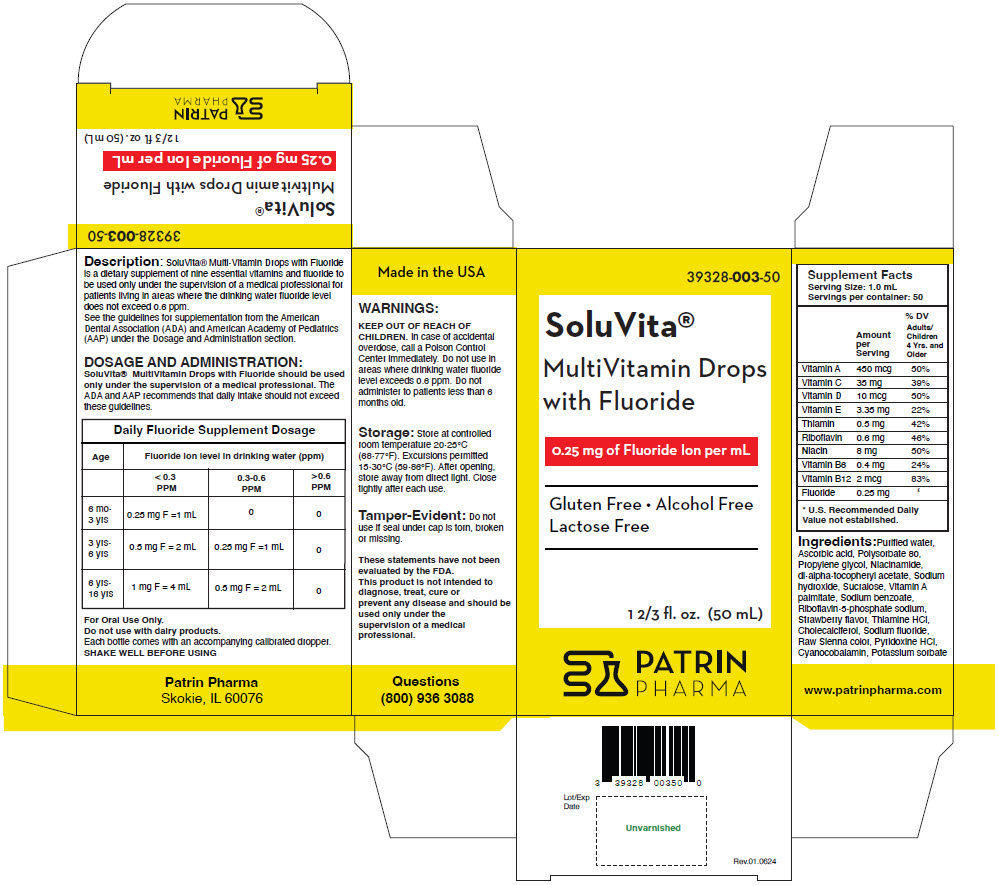 DRUG LABEL: SoluVita Multivitamin Drops with Fluoride
NDC: 39328-003 | Form: LIQUID
Manufacturer: Patrin Pharma
Category: other | Type: DIETARY SUPPLEMENT
Date: 20250417

ACTIVE INGREDIENTS: Vitamin A palmitate 450 ug/1 mL; Ascorbic acid 35 mg/1 mL; Cholecalciferol 10 ug/1 mL; .ALPHA.-TOCOPHEROL ACETATE, DL- 3.35 mg/1 mL; Thiamine Hydrochloride 0.5 mg/1 mL; RIBOFLAVIN 5'-PHOSPHATE SODIUM DIHYDRATE 0.6 mg/1 mL; Niacinamide 8 mg/1 mL; Pyridoxine Hydrochloride 0.4 mg/1 mL; Cyanocobalamin 2 ug/1 mL; Sodium fluoride 0.25 mg/1 mL
INACTIVE INGREDIENTS: Water; Polysorbate 80; Propylene glycol; Sodium hydroxide; Sucralose; Sodium benzoate; STRAWBERRY; CARAMEL; Potassium sorbate

SoluVita® Multivitamin Drops with Fluoride

Description

SoluVita® Multi-Vitamin Drops with Fluoride is a dietary supplement of nine essential vitamins and fluoride to be used only under the supervision of a medical professional for patients living in areas where the drinking water fluoride level does not exceed 0.6 ppm.

See the guidelines for supplementation from the American Dental Association (ADA) and American Academy of Pediatrics (AAP) under the Dosage and Administration section.

DOSAGE AND ADMINISTRATION

SoluVita® MultiVitamin Drops with Fluoride should be used only under the supervision of a medical professional. The ADA and AAP recommends that daily intake should not exceed these guidelines.

Daily Fluoride Supplement Dosage
Age | Fluoride ion level in drinking water (ppm)
 | < 0.3 PPM | 0.3-0.6 PPM | > 0.6 PPM
6 mo-3 yrs | 0.25 mg F =1 mL | 0 | 0
3 yrs-6 yrs | 0.5 mg F = 2 mL | 0.25 mg F =1 mL | 0
6 yrs-16 yrs | 1 mg F = 4 mL | 0.5 mg F = 2 mL | 0

For Oral Use Only.

Do not use with dairy products.

Each bottle comes with an accompanying calibrated dropper.

SHAKE WELL BEFORE USING

WARNINGS

KEEP OUT OF REACH OF CHILDREN. In case of accidental overdose, call a Poison Control Center immediately. Do not use in areas where drinking water fluoride level exceeds 0.6 ppm. Do not administer to patients less than 6 months old.

Storage

Store at controlled room temperature 20-25°C (68-77°F). Excursions permitted 15-30°C (59-86°F). After opening, store away from direct light. Close tightly after each use.

Tamper-Evident

Do not use if seal under cap is torn, broken or missing.

These statements have not been evaluated by the FDA.

This product is not intended to diagnose, treat, cure or prevent any disease and should be used only under the supervision of a medical professional.

HEALTH CLAIM

Supplement Facts
Serving Size: 1.0 mL
Servings per container: 50
 | Amount per Serving | % DV Adults/Children 4 Yrs. and Older
Vitamin A | 450 mcg | 50%
Vitamin C | 35 mg | 39%
Vitamin D | 10 mcg | 50%
Vitamin E | 3.35 mg | 22%
Thiamin | 0.5 mg | 42%
Riboflavin | 0.6 mg | 46%
Niacin | 8 mg | 50%
Vitamin B6 | 0.4 mg | 24%
Vitamin B12 | 2 mcg | 83%
Fluoride | 0.25 mg | [U.S. Recommended Daily Value not established.]

Ingredients

Purified water, Ascorbic acid, Polysorbate 80, Propylene glycol, Niacinamide, dl-alpha-tocopheryl acetate, Sodium hydroxide, Sucralose, Vitamin A palmitate, Sodium benzoate, Riboflavin-5-phosphate sodium, Strawberry flavor, Thiamine HCl, Cholecalciferol, Sodium fluoride, Raw Sienna color, Pyridoxine HCl, Cyanocobalamin, Potassium sorbate

Questions

(800) 936 3088

HEALTH CLAIM

Made in the USA

Patrin Pharma
Skokie, IL 60076

www.patrinpharma.com

PRINCIPAL DISPLAY PANEL - 50 mL Bottle Carton

39328-003-50

SoluVita®
MultiVitamin Drops
with Fluoride

0.25 mg of Fluoride Ion per mL

Gluten Free • Alcohol Free
Lactose Free

1 2/3 fl. oz. (50 mL)

PATRIN
PHARMA